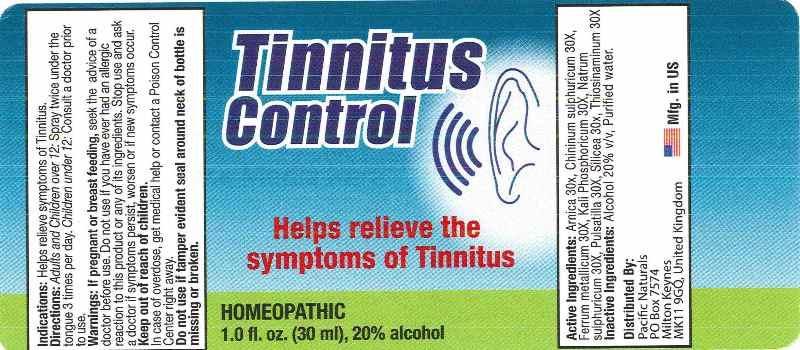 DRUG LABEL: TINNITUS CONTROL
NDC: 43695-0009 | Form: LIQUID
Manufacturer: Pacific Naturals
Category: homeopathic | Type: HUMAN OTC DRUG LABEL
Date: 20141014

ACTIVE INGREDIENTS: ARNICA MONTANA 30 [hp_X]/1 mL; QUININE SULFATE 30 [hp_X]/1 mL; IRON 30 [hp_X]/1 mL; POTASSIUM PHOSPHATE, DIBASIC 30 [hp_X]/1 mL; SODIUM SULFATE 30 [hp_X]/1 mL; PULSATILLA VULGARIS 30 [hp_X]/1 mL; SILICON DIOXIDE 30 [hp_X]/1 mL; ALLYLTHIOUREA 30 [hp_X]/1 mL
INACTIVE INGREDIENTS: WATER; ALCOHOL

DRUG FACTS:

ACTIVE INGREDIENTS:

ARNICA MONTANA 30X, CHININUM SULPHURICUM 30X, FERRUM METALLICUM 30X, KALI PHOSPHORICUM 30X, NATRUM SULPHURICUM 30X, PULSATILLA (VULGARIS) 30X, SILICEA 30X, THIOSINAMINUM 30X

INDICATIONS:

Helps relieve symptoms of Tinnitus.

WARNINGS:

If pregnant or breast-feeding, seek the advice of a doctor before use. Do not use if you have ever had an allergic reaction to this product or any of its ingredients. Stop use and ask a doctor if symptoms persist, worsen or if new symptoms occur.

Keep out of reach of children. In case of overdose, get medical help or contact a Poison Control Center right away.

Do not use if tamper evident seal around neck of bottle is missing or broken.

Keep out of reach of children. In case of overdose, get medical help or contact a Poison Control Center right away.

DIRECTIONS:

Adults and Children over 12: Spray twice under the tongue 3 times per day.

Children under 12: Consult a doctor prior to use.

INDICATIONS:

Helps relieve symptoms of Tinnitus.

INACTIVE INGREDIENTS:

Alcohol 20% v/v, Purified water.

QUESTIONS:

Distributed by:

Pacific Naturals

PO Box 7574

Milton Keynes

MK11 9GQ, United Kingdom

PACKAGE LABEL DISPLAY:

Tinnitus

Control

Helps relieve the

symptoms of Tinnitus

HOMEOPATHIC

1.0 fl. oz. (30 ml), 20% alcohol